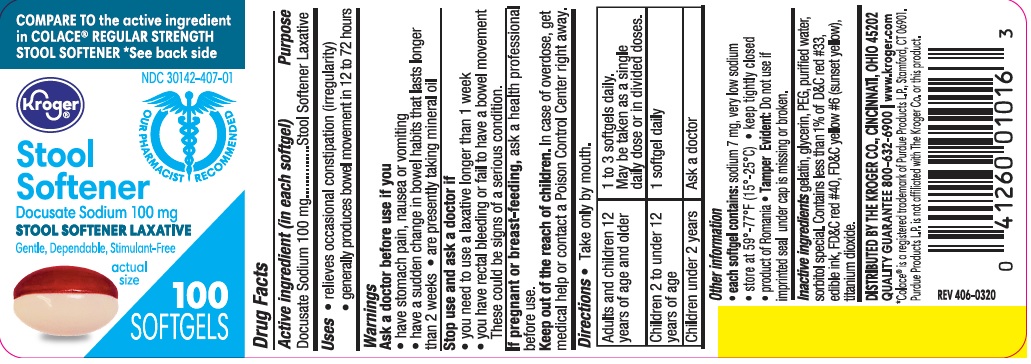 DRUG LABEL: Stool Softener
NDC: 30142-407 | Form: CAPSULE, LIQUID FILLED
Manufacturer: KROGER COMPANY
Category: otc | Type: HUMAN OTC DRUG LABEL
Date: 20231023

ACTIVE INGREDIENTS: DOCUSATE SODIUM 100 mg/1 1
INACTIVE INGREDIENTS: TITANIUM DIOXIDE; D&C RED NO. 33; POLYETHYLENE GLYCOL 400; FD&C RED NO. 40; GELATIN; GLYCERIN; SORBITOL; WATER; FD&C YELLOW NO. 6; MANNITOL

kro 406

Active ingredient (in each softgel)

Docusate Sodium 100 mg

Purpose

Stool Softener Laxative

Uses

- relieves occasional constipation (irregularity)

- generally produces bowel movement in 12 to 72 hours

Warnings

Ask a doctor before use if you

• have stomach pain, nausea or vomiting

• have a sudden change in bowel habits that lasts longer than 2 weeks

• are presently taking mineral oil

Stop use and ask a doctor if

• you need to use a laxative longer than 1 week

• you have rectal bleeding or fail to have a bowel movement. These

could be signs of a serious condition.

If pregnant or breast-feeding, ask a health professional before use.

Keep out of reach of children. In case of overdose, get medical help or contact a Poison Control Center right away.

Directions

- Take only by mouth.

Adults and children 12 years of age and older | 1 to 3 capsules daily. May be taken as a single daily dose or in divided doses.
Children 2 to under 12 years of age | 1 capsule daily
Children under 2 years | Ask a doctor

Other information

• each softgel contains: sodium 7 mg. very low sodium

• store at 59°-77°F (15°-25°C)

• keep tightly closed

• product of Romania

• Tamper Evident: Do not use if imprinted seal under cap is missing or broken.

Inactive ingredients

gelatin, glycerin, PEG, purified water, sorbitol special. Contains less that 1% of D&C red #33, edible ink, FD&C red #40, FD&C yellow #6 (sunset yellow), titanium dioxide